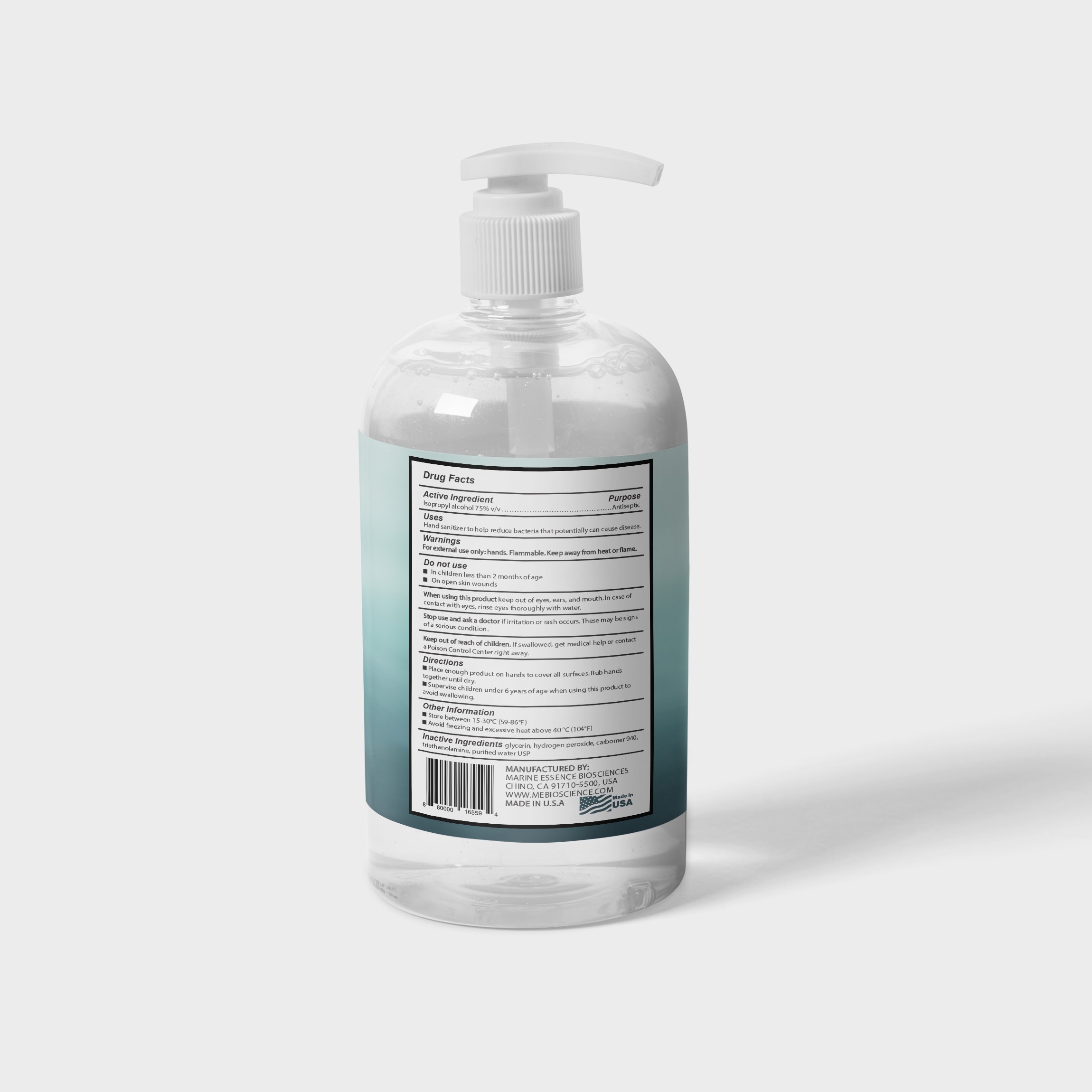 DRUG LABEL: Isopropyl Alcohol
NDC: 73764-001 | Form: GEL
Manufacturer: Marine Essence Biosciences Corporation of USA
Category: otc | Type: HUMAN OTC DRUG LABEL
Date: 20200603

ACTIVE INGREDIENTS: ISOPROPYL ALCOHOL 75.8 mL/100 mL
INACTIVE INGREDIENTS: TROLAMINE; HYDROGEN PEROXIDE; WATER; GLYCERIN; CARBOMER 940

Isopropyl Alcohol Hand Sanitizer

Active Ingredient[s]

Isopropyl alcohol 75% v/v ……………………………………..………………………………………………………………………...Antiseptic

PURPOSE

Hand sanitizer to help reduce bacteria that potentially can cause disease.

DO NOT USE

In children less than 2 months of age

On open skin wounds

When using this product keep out of eyes, ears, and mouth. In case of contact with eyes, rinse eyes thoroughly with water.

Stop use and ask a doctor if irritation or rash occurs. These may be signs of a serious condition.

Keep out of reach of children. If swallowed, get medical help or contact a Poison Control Center right away.

Keep out of reach of children. If swallowed, get medical help or contact a Poison Control Center right away.

Directions

Place enough product on hands to cover all surfaces. Rub hands together until dry.

Supervise children under 6 years of age when using this product to avoid swallowing.

OTHER SAFETY INFORMATION

Store between 15-30C (59-86F)

Avoid freezing and excessive heat above 40C (104F)

INACTIVE INGREDIENT

glycerin, hydrogen peroxide, carbomer 940, triethanolamine, purified water USP

WARNINGS

For external use only: hands. Flammable. Keep away from heat or flame.

DOSAGE AND ADMINISTRATION

Topical - Administration to a particular spot on the outer surface of the body.

DOSAGE FORMS AND STRENGTHS

Gel form

INDICATIONS AND USAGE

To help reduce bacteria on the hands that can potentially cause disease.